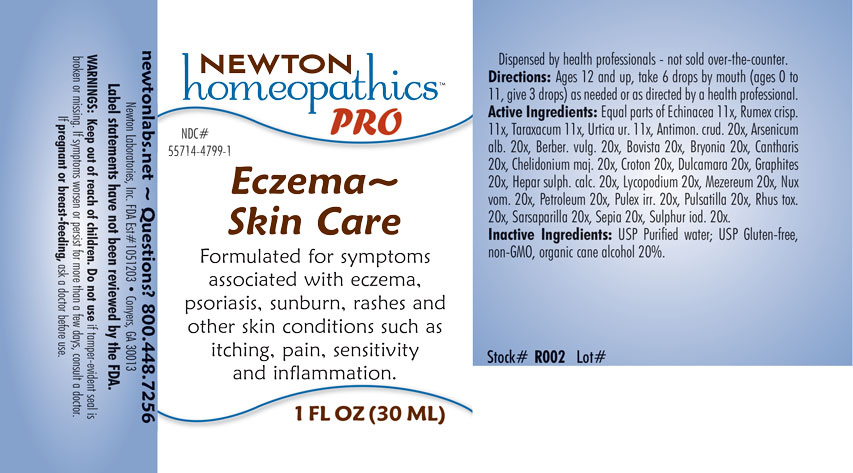 DRUG LABEL: Eczema - Skin Care
NDC: 55714-4799 | Form: LIQUID
Manufacturer: Newton Laboratories, Inc.
Category: homeopathic | Type: HUMAN OTC DRUG LABEL
Date: 20201202

ACTIVE INGREDIENTS: SMILAX ORNATA ROOT 20 [hp_X]/1 mL; ANTIMONY TRISULFIDE 20 [hp_X]/1 mL; ARSENIC TRIOXIDE 20 [hp_X]/1 mL; BERBERIS VULGARIS ROOT BARK 20 [hp_X]/1 mL; LYCOPERDON UTRIFORME FRUITING BODY 20 [hp_X]/1 mL; BRYONIA ALBA ROOT 20 [hp_X]/1 mL; LYTTA VESICATORIA 20 [hp_X]/1 mL; CHELIDONIUM MAJUS 20 [hp_X]/1 mL; CROTON TIGLIUM SEED 20 [hp_X]/1 mL; SOLANUM DULCAMARA TOP 20 [hp_X]/1 mL; GRAPHITE 20 [hp_X]/1 mL; CALCIUM SULFIDE 20 [hp_X]/1 mL; LYCOPODIUM CLAVATUM SPORE 20 [hp_X]/1 mL; DAPHNE MEZEREUM BARK 20 [hp_X]/1 mL; STRYCHNOS NUX-VOMICA SEED 20 [hp_X]/1 mL; KEROSENE 20 [hp_X]/1 mL; PULEX IRRITANS 20 [hp_X]/1 mL; ANEMONE PULSATILLA 20 [hp_X]/1 mL; TOXICODENDRON PUBESCENS LEAF 20 [hp_X]/1 mL; SEPIA OFFICINALIS JUICE 20 [hp_X]/1 mL; SULFUR IODIDE 20 [hp_X]/1 mL; ECHINACEA, UNSPECIFIED 11 [hp_X]/1 mL; RUMEX CRISPUS ROOT 11 [hp_X]/1 mL; TARAXACUM OFFICINALE 11 [hp_X]/1 mL; URTICA URENS 11 [hp_X]/1 mL
INACTIVE INGREDIENTS: ALCOHOL; WATER

Eczema 4799L

INDICATIONS & USAGE SECTION

Formulated for symptoms associated with eczema, psoriasis, sunburn, rashes and other skin conditions such as itching, pain, sensitivity and inflammation.

DOSAGE & ADMINISTRATION SECTION

Directions: ges 12 and up, take 6 drops by mouth (ages 0 to 11, give 3 drops) as needed or as directed by a health professional.

OTC - ACTIVE INGREDIENT SECTION

Active Ingredients: Equal parts of Echinacea 11x, Rumex crispus 11x, Taraxacum officinale 11x, Urtica urens 11x, Antimonium crudum 20x, Arsenicum album 20x, Berberis vulgaris 20x, Bovista 20x, Bryonia 20x, Cantharis 20x, Chelidonium majus 20x, Croton tiglium 20x, Dulcamara 20x, Graphites 20x, Hepar sulphuris calcareum 20x, Lycopodium clavatum 20x, Mezereum 20x, Nux vomica 20x, Petroleum 20x, Pulex irritans 20x, Pulsatilla 20x, Rhus toxicodendron 20x, Sarsaparilla 20x, Sepia 20x, Sulphur iodatum 20x.

OTC - PURPOSE SECTION

Formulated for symptoms associated with eczema, psoriasis, sunburn, rashes and other skin conditions such as itching, pain, sensitivity and inflammation.

INACTIVE INGREDIENT SECTION

Inactive Ingredients: USP Purified Water; USP Gluten-free, non-GMO, organic cane alcohol 20%.

QUESTIONS SECTION

newtonlabs.net - Questions? 800.448.7256

Newton Laboratories, Inc. FDA Est # 1051203 - Conyers, GA 30013

WARNINGS SECTION

WARNINGS: Keep out of reach of children. Do not use if tamper-evident seal is broken or missing. If symptoms worsen or persist for more than a few days, consult a doctor. If pregnant or breast-feeding, ask a doctor before use.

OTC - PREGNANCY OR BREAST FEEDING SECTION

If pregnant or breast-feeding, ask a doctor before use.

OTC - KEEP OUT OF REACH OF CHILDREN SECTION

Keep out of reach of children.